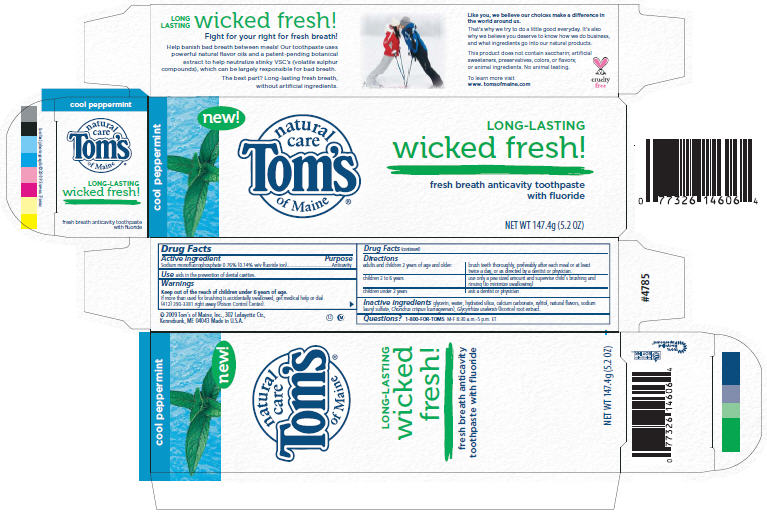 DRUG LABEL: Long-Lasting Wicked Fresh - Cool Peppermint
NDC: 51009-146 | Form: PASTE, DENTIFRICE
Manufacturer: Tom's of Maine, Inc.
Category: otc | Type: HUMAN OTC DRUG LABEL
Date: 20091109

ACTIVE INGREDIENTS: Sodium monofluorophosphate 0.0076  g/1 g
INACTIVE INGREDIENTS: Glycerin; Water; Calcium carbonate; Xylitol; Silicon Dioxide; Carrageenan; Peppermint Oil; Menthol; Sodium Lauryl Sulfate; Anise Seed; Eucalyptus Oil; Licorice; Vanillin; Cinnamyl Alcohol; Clove oil

natural care
Tom's
of Maine®

Drug Facts

Active ingredient

Sodium monofluorophosphate 0.76% (0.14% w/v fluoride ion)

Purpose

Anticavity

Use

aids in the prevention of dental cavities.

Warnings

KEEP OUT OF REACH OF CHILDREN

Keep out of the reach of children under 6 years of age.

If more than used for brushing is accidentally swallowed, get medical help or dial (412) 390-3381 right away (Poison Control Center).

Directions

adults and children 2 years of age and older: | brush teeth thoroughly, preferably after each meal or at least twice a day, or as directed by a dentist or physician.
children 2 to 6 years | use only a pea sized amount and supervise child's brushing and rinsing (to minimize swallowing)
children under 2 years | ask a dentist or physician

Inactive ingredients

glycerin, water, hydrated silica, calcium carbonate, xylitol, natural flavors, sodium lauryl sulfate, Chondrus crispus (carrageenan), Glycyrrhiza uralensis (licorice) root extract.

Questions?

1-800-FOR-TOMS M-F 8:30 a.m.-5 p.m. ET

© 2009 Tom's of Maine, Inc., 302 Lafayette Ctr.,
Kennebunk, ME 04043 Made in U.S.A.

PRINCIPAL DISPLAY PANEL - 147.4g Box

cool peppermint

new!

natural
care
Tom's
of Maine®

LONG-LASTING
wicked fresh!

fresh breath anticavity toothpaste
with fluoride

NET WT 147.4g (5.2 OZ)